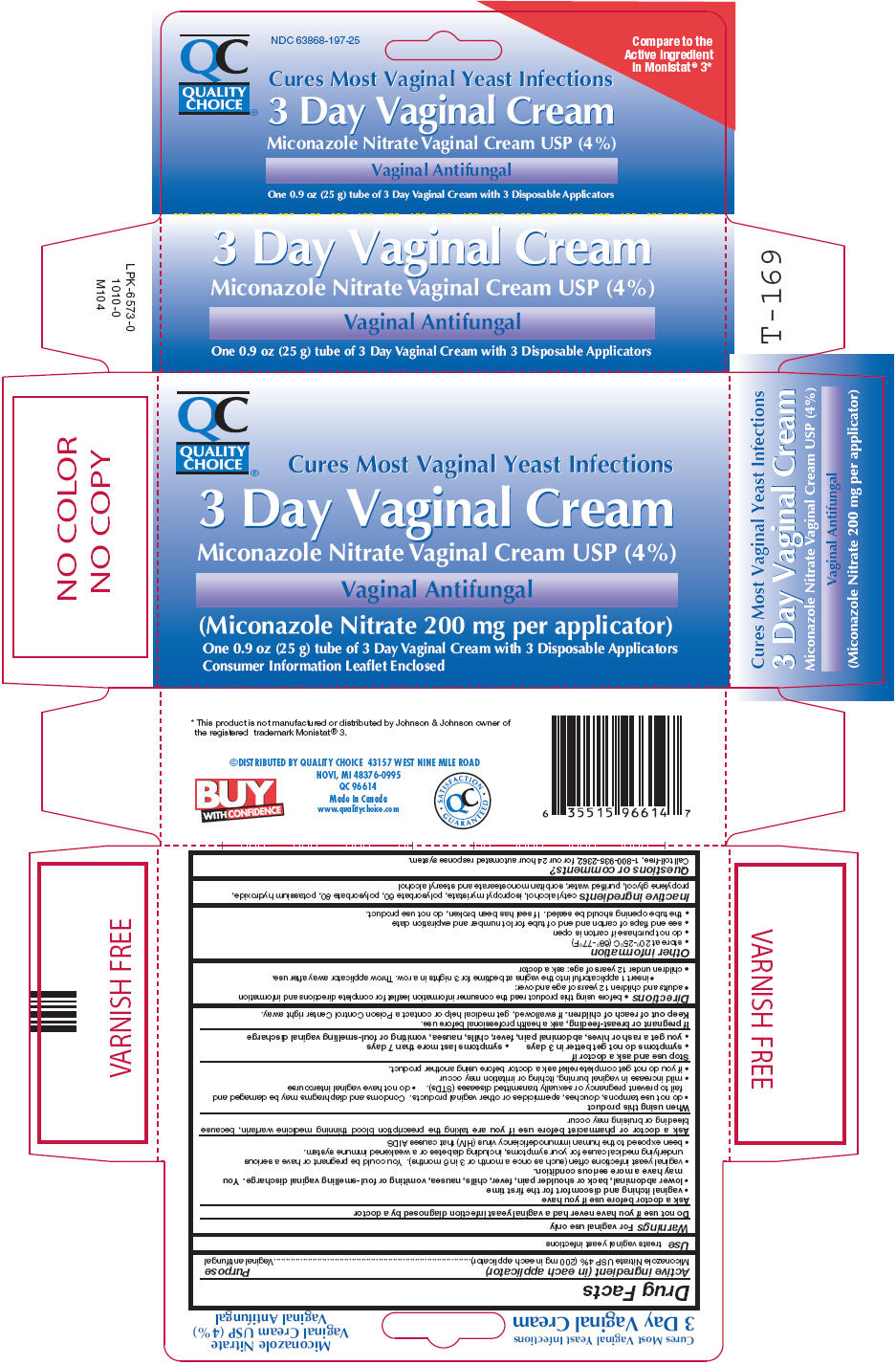 DRUG LABEL: Quality Choice 
NDC: 63868-197 | Form: CREAM
Manufacturer: Chain Drug Marketing Association
Category: otc | Type: HUMAN OTC DRUG LABEL
Date: 20130311

ACTIVE INGREDIENTS: Miconazole Nitrate 40 mg/1 g
INACTIVE INGREDIENTS: CETYL ALCOHOL; ISOPROPYL MYRISTATE; POLYSORBATE 60; POLYSORBATE 80; POTASSIUM HYDROXIDE; PROPYLENE GLYCOL; WATER; SORBITAN MONOSTEARATE; STEARYL ALCOHOL

Quality Choice®
3 Day Vaginal

Drug Facts

Active ingredient (in each applicator)

Miconazole Nitrate USP 4% (200 mg in each applicator)

Purpose

Vaginal antifungal

Use

treats vaginal yeast infections

Warnings

For vaginal use only

Do not use if you have never had a vaginal yeast infection diagnosed by a doctor

Ask a doctor before use if you have

- vaginal itching and discomfort for the first time
- lower abdominal, back or shoulder pain, fever, chills, nausea, vomiting or foul-smelling vaginal discharge. You may have a more serious condition.
- vaginal yeast infections often (such as once a month or 3 in 6 months). You could be pregnant or have a serious underlying medical cause for your symptoms, including diabetes or a weakened immune system.
- been exposed to the human immunodeficiency virus (HIV) that causes AIDS

Ask a doctor or pharmacist before use if you are taking the prescription blood thinning medicine warfarin, because bleeding or bruising may occur

When using this product

- do not use tampons, douches, spermicides or other vaginal products. Condoms and diaphragms may be damaged and fail to prevent pregnancy or sexually transmitted diseases (STDs).
- do not have vaginal intercourse
- mild increase in vaginal burning, itching or irritation may occur
- if you do not get complete relief ask a doctor before using another product.

Stop use and ask a doctor if

- symptoms do not get better in 3 days
- symptoms last more than 7 days
- you get a rash or hives, abdominal pain, fever, chills, nausea, vomiting or foul-smelling vaginal discharge

PREGNANCY OR BREAST FEEDING

If pregnant or breast-feeding, ask a health professional before use.

Keep out of reach of children. If swallowed, get medical help or contact a Poison Control Center right away.

Directions

- before using this product read the consumer information leaflet for complete directions and information
- adults and children 12 years of age and over:
  - insert 1 applicatorful into the vagina at bedtime for 3 nights in a row. Throw applicator away after use.
- children under 12 years of age: ask a doctor

Other information

- store at 20°-25°C (68°-77°F)
- do not purchase if carton is open
- see end flaps of carton and end of tube for lot number and expiration date
- the tube opening should be sealed. If seal has been broken, do not use product.

Inactive ingredients

cetyl alcohol, isopropyl myristate, polysorbate 60, polysorbate 80, potassium hydroxide, propylene glycol, purified water, sorbitan monostearate and stearyl alcohol

Questions or comments?

Call toll-free, 1-800-935-2362, for our 24 hour automated response system.

DISTRIBUTED BY QUALITY CHOICE 43157 WEST NINE MILE ROAD
NOVI, MI 48376-0995

PRINCIPAL DISPLAY PANEL - 25 g Tube Carton

QC
QUALITY
CHOICE®

Cures Most Vaginal Yeast Infections

3 Day Vaginal Cream

Miconazole Nitrate Vaginal Cream USP (4%)

Vaginal Antifungal

(Miconazole Nitrate 200 mg per applicator)

One 0.9 oz (25 g) tube of 3 Day Vaginal Cream with 3 Disposable Applicators
Consumer Information Leaflet Enclosed